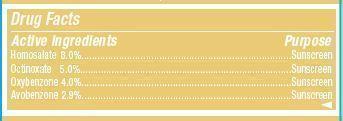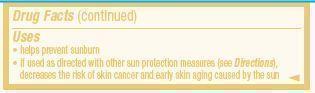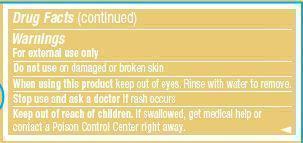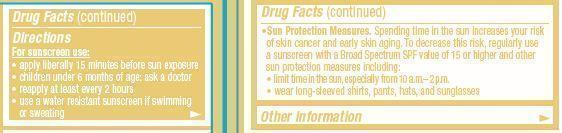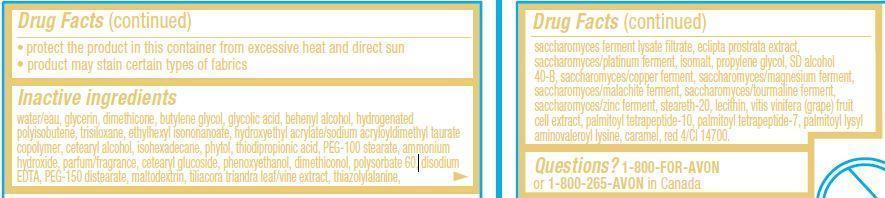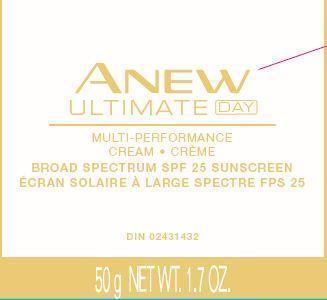 DRUG LABEL: Anew Ultimate
NDC: 10096-0323 | Form: CREAM
Manufacturer: New Avon LLC
Category: otc | Type: HUMAN OTC DRUG LABEL
Date: 20190101

ACTIVE INGREDIENTS: HOMOSALATE 80 mg/1 g; OCTINOXATE 50 mg/1 g; OXYBENZONE 40 mg/1 g; AVOBENZONE 29 mg/1 g
INACTIVE INGREDIENTS: WATER

Anew Ultimate Multi-Performance Day Cream SPF 25

Active Ingredients
Homosalate 8.0%............................
Octinoxate 5.0%..............................
Oxybenzone 4.0%.........................
Avobenzone 2.9%...........................

Purpose
............... Sunscreen
............... Sunscreen
.............. Sunscreen

.............. Sunscreen

Uses

- helps prevent sunburn
- if used as directed with other sun protection measures (see Directions), decreases the risk of skin cancer and early skin aging caused by the sun

Warnings
For external use only

Do not use on damaged or broken skin

When using this product keep out of eyes. Rinse with water to remove.

Stop use and ask a doctor if rash occurs

Keep out of reach of children. If swallowed, get medical help or contact a Poison Control Center right away.

Directions

For sunscreen use:

- apply liberally 15 minutes before sun exposure
- children under 6 month of age:ask a doctor
- reapply at least every 2 hours
- use a water resistant sunscreen if swimming or sweating
- Sun Protection Measures. Spending time in the sun increases your risk of skin cancer and early skin aging. To decrease this risk, regularly use a sunscreen with a Broad Spectrum SPF value of 15 or higher and other sun protection measures including:
  • limit time in the sun, especially from 10 a.m. – 2 p.m.
  • wear long-sleeved shirts, pants, hats, and sunglasses

Other Information

- protect the product in this container from excessive heat and direct sun
- product may stain certain types of fabrics

Inactive ingredients:
water/eau, glycerin, dimethicone, butylene glycol, glycolic acid, behenyl alcohol, hydrogenated polyisobutene, trisiloxane, ethylhexyl isononanoate, hydroxyethyl acrylate/sodium acryloyldimethyl taurate copolymer, cetearyl alcohol, isohexadecane, phytol, thiodipropionic acid, PEG-100 stearate, ammonium hydroxide, parfum/fragrance, cetearyl glucoside, phenoxyethanol, dimethiconol, polysorbate 60, disodium EDTA, PEG-150 distearate, maltodextrin, tiliacora triandra leaf/vine extract, thiazolylalanine, saccharomyces ferment lysate filtrate, eclipta prostrata extract, saccharomyces/platinum ferment, isomalt, propylene glycol, SD alcohol 40-B, saccharomyces/copper ferment, saccharomyces/magnesium ferment, saccharomyces/malachite ferment, saccharomyces/tourmaline ferment, saccharomyces/zinc ferment, steareth-20, lecithin, vitis vinifera (grape) fruit cell extract, palmitoyl tetrapeptide-10, palmitoyl tetrapeptide-7, palmitoyl lysyl aminovaleroyl lysine, caramel, red 4/CI 14700.

Questions?
1-800-FOR-AVON or 1-800-265-AVON in Canada